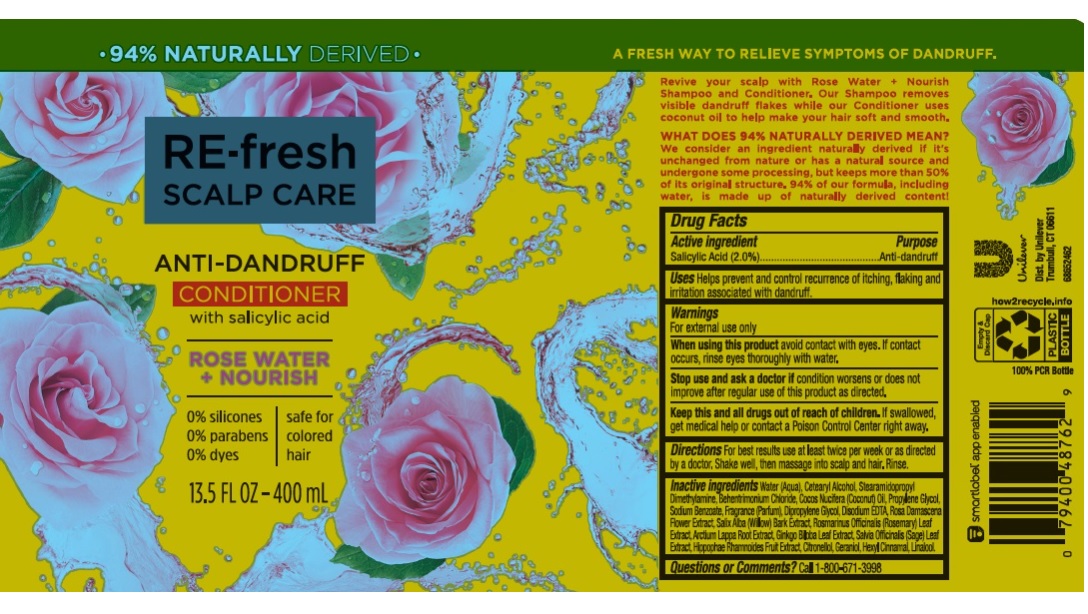 DRUG LABEL: RE-fresh Scalp Care
NDC: 64942-1929 | Form: LIQUID
Manufacturer: Conopco, Inc. d/b/a/ Unilever
Category: otc | Type: HUMAN OTC DRUG LABEL
Date: 20241107

ACTIVE INGREDIENTS: SALICYLIC ACID 2 g/100 mL
INACTIVE INGREDIENTS: ROSEMARY; SAGE; ROSA X DAMASCENA FLOWER; HIPPOPHAE RHAMNOIDES FRUIT; SALIX ALBA BARK; GERANIOL; WATER; CETOSTEARYL ALCOHOL; STEARAMIDOPROPYL DIMETHYLAMINE; BEHENTRIMONIUM CHLORIDE; COCONUT OIL; ARCTIUM LAPPA ROOT; GINKGO; PROPYLENE GLYCOL; SODIUM BENZOATE; DIPROPYLENE GLYCOL; EDETATE DISODIUM ANHYDROUS; .BETA.-CITRONELLOL, (R)-; .ALPHA.-HEXYLCINNAMALDEHYDE; LINALOOL, (+/-)-

RE-fresh Scalp Care Rose Water + Nourish Anti-Dandruff Conditioner

Drug Facts

Active ingredient

Salicylic Acid (2.0%)

Purpose

Anti-dandruff

Use

Helps prevent and control recurrence of itching, flaking and irritation associated with dandruff.

Warnings

For external use only
When using this product Avoid contact with eyes. If contact occurs, rinse eyes thoroughly with water.
Stop use and ask a doctor if: Condition worsens or does not improve after regular use of this product as directed.

KEEP OUT OF REACH OF CHILDREN

Keep this and all drugs out of reach of children. If swallowed, get medical help or contact a Poison Control Center right away.

Directions

For best results use at least twice per week or as directed by a doctor. Massage into scalp and hair. Rinse.

Inactive Ingredients

Water (Aqua), Cetearyl Alcohol, Stearamidopropyl Dimethylamine, Behentrimonium Chloride, Cocos Nucifera (Coconut) Oil, Propylene Glycol, Sodium Benzoate, Fragrance (Parfum), Dipropylene Glycol, Disodium EDTA, Rosa Damascena Flower Extract, Salix Alba (Willow) Bark Extract, Rosmarinus Officinalis (Rosemary) Leaf Extract, Arctium Lappa Root Extract, Ginkgo Biloba Leaf Extract, Salvia Officinalis (Sage) Leaf Extract, Hippophae Rhamnoides Fruit Extract, Citronellol, Geraniol, Hexyl Cinnamal, Linalool.

Questions/comments?

Call toll-free 1-800-671-3998